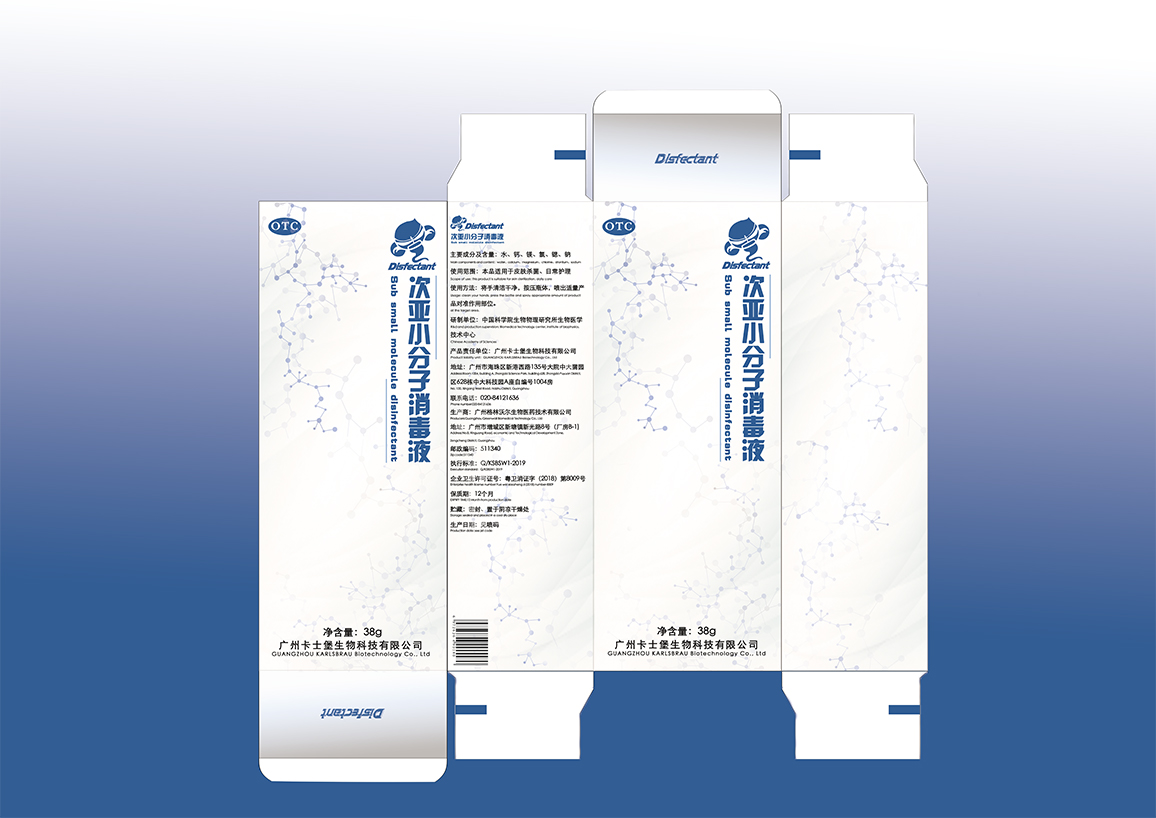 DRUG LABEL: Sub small molecule disinfectant
NDC: 41856-001 | Form: LIQUID
Manufacturer: GUANGZHOU KARLSBRAU Biotechnology Co., Ltd
Category: otc | Type: HUMAN OTC DRUG LABEL
Date: 20200201

ACTIVE INGREDIENTS: CHLORINE 0.0076 g/38 g; CALCIUM 0.038 g/38 g
INACTIVE INGREDIENTS: STRONTIUM; MAGNESIUM; SODIUM; WATER

DOSAGE AND ADMINISTRATION

EXPIRY TIME:12 Month from production date

Storage: sealed and placed in a cool dry place

WARNINGS

for external use, avoid oral administration;

if you feel any discomfort after using, please stop using;

INACTIVE INGREDIENT

water, magnesium, strontium, sodium

INDICATIONS AND USAGE

Scope of use: this product is suitable for skin sterilization, daily care

Usage: clean your hands, press the bottle and spray appropriate amount of product at the target area.

keep out of reach of children to prevent accidental ingestion.

PURPOSE

Microbe categories: staphylococcus aureus, candida albicans, escherichia coli, etc

ACTIVE INGREDIENT

chlorine, calcium